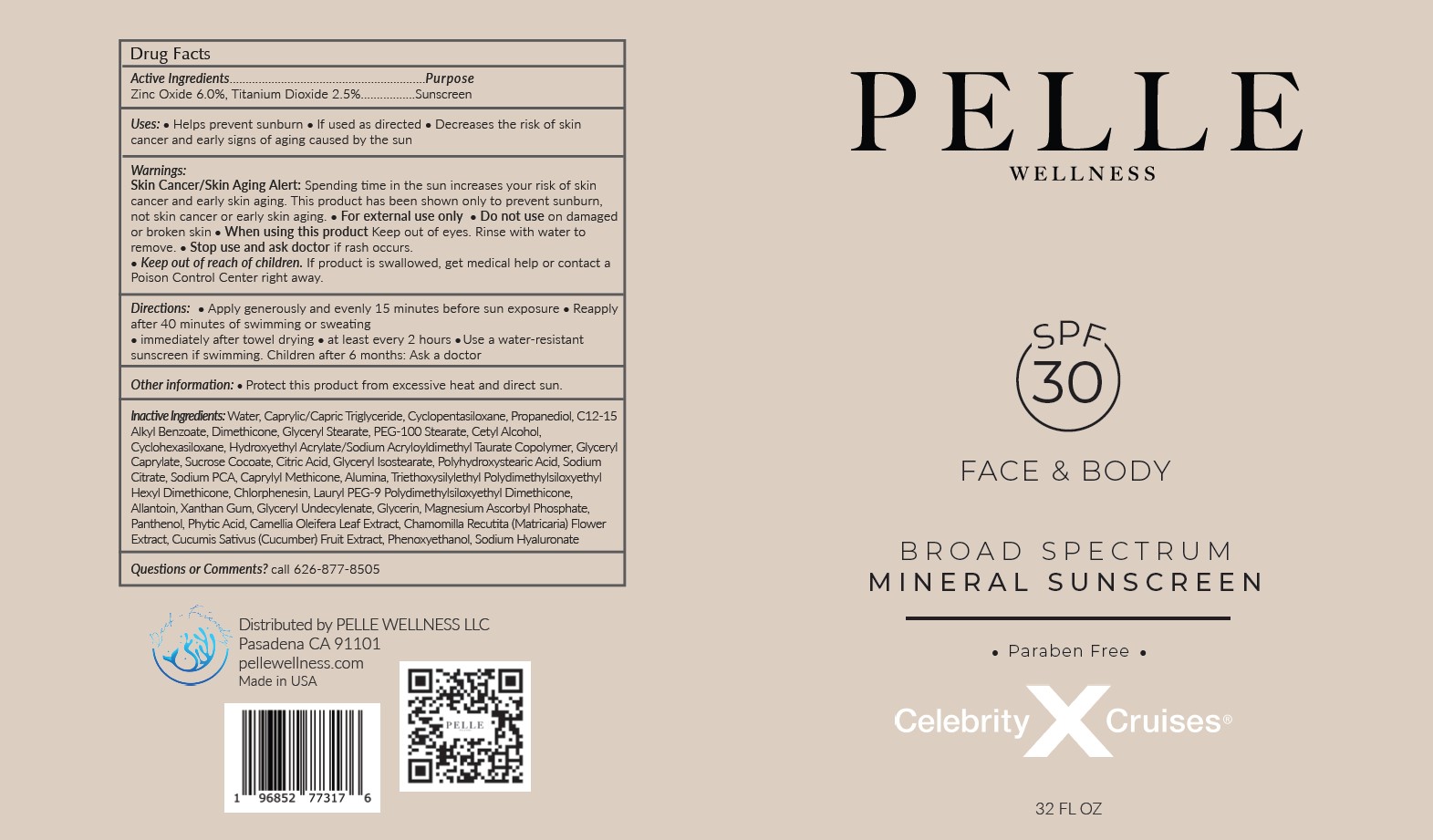 DRUG LABEL: PELLE WELLNESS SPF 30 FACE AND BODY BROAD SPECTRUM MINERAL SUNSCREEN
NDC: 83625-102 | Form: CREAM
Manufacturer: Pelle Wellness LLC
Category: otc | Type: HUMAN OTC DRUG LABEL
Date: 20230826

ACTIVE INGREDIENTS: TITANIUM DIOXIDE 2.5 g/100 mL; ZINC OXIDE 6 g/100 mL
INACTIVE INGREDIENTS: FYTIC ACID; DIMETHICONE; CAPRYLYL TRISILOXANE; CYCLOMETHICONE 6; MATRICARIA CHAMOMILLA FLOWERING TOP; SODIUM PYRROLIDONE CARBOXYLATE; GLYCERYL CAPRYLATE; ALUMINUM OXIDE; GLYCERYL MONOSTEARATE; HYALURONATE SODIUM; PHENOXYETHANOL; WATER; GLYCERIN; CYCLOMETHICONE 5; ALKYL (C12-15) BENZOATE; PROPANEDIOL; PEG-100 STEARATE; CETYL ALCOHOL; HYDROXYETHYL ACRYLATE/SODIUM ACRYLOYLDIMETHYL TAURATE COPOLYMER (45000 MPA.S AT 1%); CITRIC ACID MONOHYDRATE; SODIUM CITRATE; XANTHAN GUM; TRIETHOXYSILYLETHYL POLYDIMETHYLSILOXYETHYL HEXYL DIMETHICONE; LAURYL PEG-9 POLYDIMETHYLSILOXYETHYL DIMETHICONE; CHLORPHENESIN; ALLANTOIN; POLYHYDROXYSTEARIC ACID (2300 MW); SUCROSE COCOATE; GLYCERYL 1-UNDECYLENATE; PANTHENOL; CAMELLIA OLEIFERA LEAF; CUCUMIS SATIVUS WHOLE; MAGNESIUM ASCORBYL PHOSPHATE; MEDIUM-CHAIN TRIGLYCERIDES; GLYCERYL ISOSTEARATE

Pelle Wellness (as PLD) - SPF 30 Face & Body Broad Spectrum Mineral Sunscreen (83625-102)

ACTIVE INGREDIENTS

ZINC OXIDE 6.0%

TITANIUM DIOXIDE 2.5%

PURPOSE

SUNSCREEN

USES

- Helps prevent sunburn
- If used as directed
- Decreases the risk of skin cancer and early signs of aging caused by the sun

WARNINGS

Skin Cancer/Skin Aging Alert: Spending time in the sun increases your risk of skin cancer and early skin aging. This product has been shown only to prevent sunburn, not skin cancer or early skin aging.

- For external use only
- Do not use on damaged or broken skin
- When using this product Keep out of eyes. Rinse with water to remove.
- Stop use and ask doctor if rash occurs.

- Keep out of reach of children. If product is swallowed, get medical help or contact a Poison Control Center right away.

DIRECTIONS

- Apply generously and evenly 15 minutes before sun exposure
- Reapply after 40 minutes of swimming or sweating
- immediately after towel drying
- at least every 2 hours
- Use a water-resistant sunscreen if swimming.

Children after 6 months: Ask a doctor

STORAGE AND HANDLING

- Protect this product from excessive heat and direct sun.

INACTIVE INGREDIENTS

Water, Caprylic/Capric Triglyceride, Cyclopentasiloxane, Propanediol, C12-15 Alkyl Benzoate, Dimethicone, Glyceryl Stearate, PEG-100 Stearate, Cetyl Alcohol, Cyclohexasiloxane, Hydroxyethyl Acrylate/Sodium Acryloyldimethyl Taurate Copolymer, Glyceryl Caprylate, Sucrose Cocoate, Citric Acid, Glyceryl Isostearate, Polyhydroxystearic Acid, Sodium Citrate, Sodium PCA, Caprylyl Methicone, Alumina, Triethoxysilylethyl Polydimethylsiloxyethyl Hexyl Dimethicone, Chlorphenesin, Lauryl PEG-9 Polydimethylsiloxyethyl Dimethicone,
Allantoin, Xanthan Gum, Glyceryl Undecylenate, Glycerin, Magnesium Ascorbyl Phosphate, Panthenol, Phytic Acid, Camellia Oleifera Leaf Extract, Chamomilla Recutita (Matricaria) Flower Extract, Cucumis Sativus (Cucumber) Fruit Extract, Phenoxyethanol, Sodium Hyaluronate

Questions or Comments?

call 626-877-8505